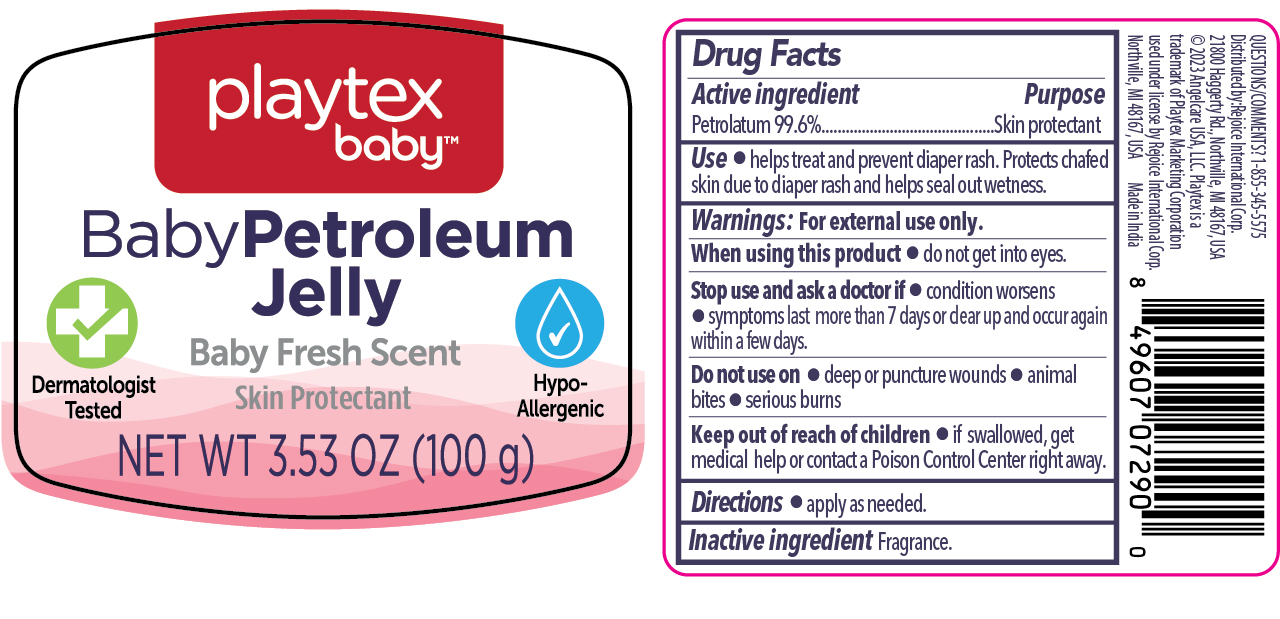 DRUG LABEL: Petroleum Jelly Baby Fresh Scent 3.53oz
NDC: 57337-162 | Form: OINTMENT
Manufacturer: Rejoice International Corp.
Category: otc | Type: HUMAN OTC DRUG LABEL
Date: 20251111

ACTIVE INGREDIENTS: PETROLATUM 99.6 g/100 g
INACTIVE INGREDIENTS: FRAGRANCE 13576

Petroleum Jelly Baby Fresh Scent 3.53oz

Active ingredient

Petrolatum 99.6%

Purpose

Skin protectant

Use

- helps treat and prevent diaper rash. Protects chafed skin due to diaper rash and helps seal out wetness.

Warnings

For external use only

When using this product do not get into eyes.

Stop use and ask a doctor if

- condition worsens
- symtoms last more than 7 days or clear up and occur again within a few days.

Do not use

- deep or puncture wounds
- animal bites
- serious burns

Keep out of reach of children

- if swallowed, get medical help or contact a Poison Control Center right away.

Directions

- apply as needed.

Inactive ingredient

Fragrance